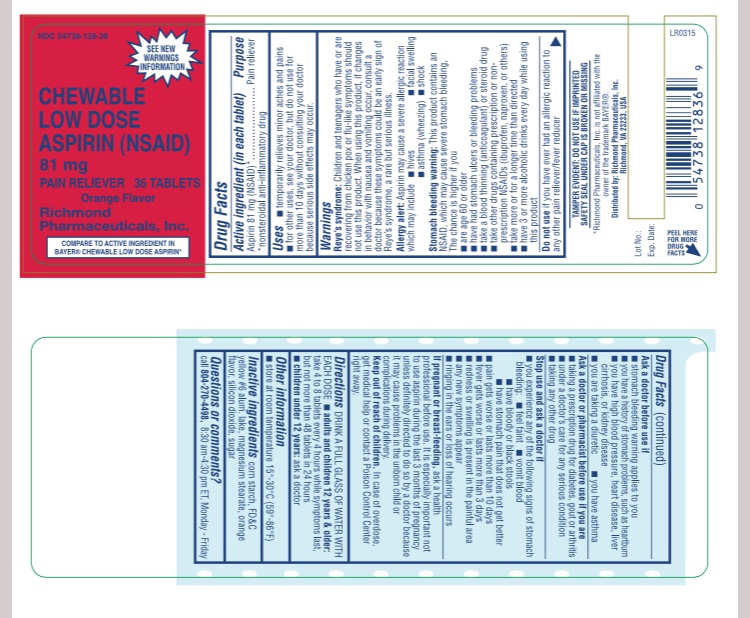 DRUG LABEL: Aspirin
NDC: 54738-128 | Form: TABLET, CHEWABLE
Manufacturer: Richmond Pharmaceuticals, Inc.
Category: otc | Type: HUMAN OTC DRUG LABEL
Date: 20171030

ACTIVE INGREDIENTS: ASPIRIN 81 mg/1 1
INACTIVE INGREDIENTS: STARCH, CORN; FD&C YELLOW NO. 6; MAGNESIUM STEARATE; ORANGE; SILICON DIOXIDE; SUCROSE

ASPIRIN 81mg

Active Ingredient

(in each tablet)

Aspirin 81 mg (NSAID) *

*nonsteroidal anti-inflammatory drug

Purpose

Pain Reliever

Use

- temporarily relieves minor aches and pains
- for other uses, see your doctor, but do not use for more than 10 days without consulting your doctor because serious side effect may occur.

Warnings

Reye’s Syndrome: Children and teenagers who have or are recovering from chicken pox or flu-like symptoms should not use this product. When using this product, if changes in behavior with nausea and vomiting occur, consult a doctor because these symptoms could be an early signs of Reye’s syndrome, a rare but serious illness.

Allergy Alert: Aspirin may cause a severe allergic reaction which may include

- hives
- asthma (wheezing)
- shock
- facial swelling
  Stomach Bleeding Warning: This product contains an NSAID, which may cause severe stomach bleeding. The chance is higher if your child
- has had stomach ulcers or bleeding problems
- take a blood-thinning (anticoagulant) or steroid drug
- takes other drugs containing prescription or nonprescription NSAIDs (ibuprofen, naproxen, others)
- takes more or for a longer time than directed
  Do not use
- if the child has ever had an allergic reaction to any other pain reliever / fever reducer
- for at least 7 days after tonsillectomy or oral surgery
  Ask a doctor before use if
- stomach bleeding warning applies to your child
- child has a history of stomach problems, such as heartburn
- child has not been drinking fluids
- child has lost a lot of fluid due to vomiting and diarrhea
- child has high blood pressure, heart disease, lever cirrhosis, or kidney disease
- child is taking a diuretic
- child has asthma
  Ask a doctor or pharmacist before use if the child is
- taking a prescription drug for diabetes, gout or arthritis
- taking any other drug
- under a doctor’s care for any serious condition
  Stop use and ask a doctor if
- child experiences any of the following signs of stomach bleeding:
- feels faint
- vomits blood
- has bloody or black stools
- has stomach pain that does not get better
- pain gets worse or lasts more than 5 days
- any new symptoms appear
- redness or swelling is present in the painful area
- ringing in the ears or a loss of hearing occurs
  If pregnant or breast-feeding, ask a health professional before use. It is especially important not to use aspirin during the last 3 months of pregnancy unless definitely directed to do so by a doctor because it may cause problems in the unborn child or complications during delivery.

Keep out of reach of children.

In case of overdose, get medical help or contact a Poison Control Center right away.

Directions

- DRINK A FULL GLASS OF WATER WITH EACH DOSE
- adults and children 12 years and older : take 4 to 8 tablets every 4 hours while symptoms last, but not more than 48 tablets in 24 hours.
- Children under 12 years: ask a doctor

Other Information

- store at 15-30 °C (59-86 °F)

Inactive Ingredients

corn starch, FD&C Yellow #6 alum. lake, magnesium stearate, orange flavor, silicon dioxide, sugar

Questions or Comments

Call 804-270-4498, 8.30am – 4.30 pm ET Monday-Friday

TAMPER EVIDENT: DO NOT USE IF IMPRINTED SAFETY SEAL UNDER CAP IS BROKEN OR MISSING

PACKAGE LABEL.PRINCIPAL DISPLAY PANEL

NDC: 54738-128-36 – 36 COUNT